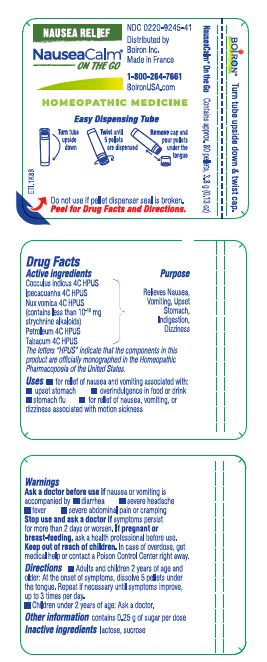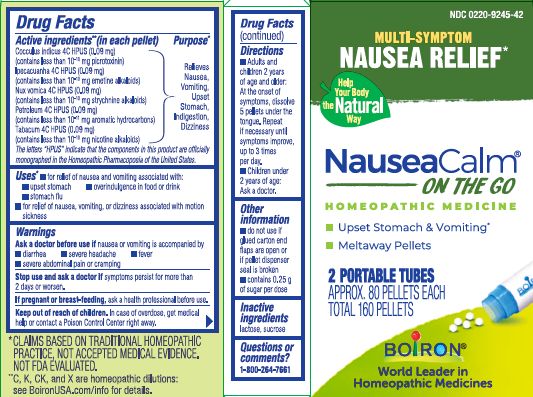 DRUG LABEL: NauseaCalm
NDC: 0220-9245 | Form: PELLET
Manufacturer: Boiron
Category: homeopathic | Type: HUMAN OTC DRUG LABEL
Date: 20240731

ACTIVE INGREDIENTS: TOBACCO LEAF 4 [hp_C]/1 1; KEROSENE 4 [hp_C]/1 1; IPECAC 4 [hp_C]/1 1; STRYCHNOS NUX-VOMICA SEED 4 [hp_C]/1 1; ANAMIRTA COCCULUS SEED 4 [hp_C]/1 1
INACTIVE INGREDIENTS: SUCROSE; LACTOSE, UNSPECIFIED FORM

NauseaCalm Pellets

Active ingredients **

Cocculus indicus 4C HPUS (0.09 mg) (contains less than 10^-10 mg picrotoxinin)

Ipecacuanha 4C HPUS (0.09 mg) (contains less than 10^-10 mg emetine alkaloids)

Nux Vomica 4C HPUS (0.09 mg) (contains less than 10^-10 mg strychnine alkaloids)

Petroleum 4C HPUS (0.09 mg) (contains less than 10^-11 mg aromatic hydrocarbons)

Tabacum 4C HPUS (0.09 mg) (contains less than 10-^10 mg nicotine alkaloids)

The letters "HPUS" indicate that the components in this product are officially monographed in the Homeopathic Pharmacopoeia of the United States.

Purpose*

Relieves Nausea, Vomiting, Upset Stomach, Indigestion, Dizziness

Uses*

- for relief of nausea and vomiting associated with:
- upset stomach
- overindulgence in food or drink
- stomach flu

- for relief of nausea, vomiting, or dizziness associated with motion sickness

Ask a doctor before use if nausea or vomiting is accompanied by

- diarrhea
- severe headache
- fever
- severe abdominal pain or cramping

Stop use and ask a doctor if symptoms persist for more than 2 days or worsen.

PREGNANCY OR BREAST FEEDING

If pregnant or breast-feeding, ask a health professional before use.

Keep out of reach of children. In case of accidental overdose, get medical help or contact a Poison Control Center right away.

DOSAGE AND ADMINISTRATION

- Adults and children 2 years of age and older: At the onset of symptoms, dissolve 5 pellets under the tongue. Repeat if necessary until symptoms improve, up to 3 times per day.
- Children under 2 years of age: Ask a doctor.

INACTIVE INGREDIENT

lactose. sucrose

QUESTIONS

1-800-264-7661

Made in France

Distributed by Boiron, Inc. Newtown Square, PA 19073

- do not use if glued carton end flaps are open or if pellet dispenser seal is broken
- contains 0.25 g of sugar per dose

MULTI-SYMPTOM NAUSEA RELIEF*

2 PORTABLE TUBES

APPROX. 80 PELLETS EACH

TOTAL 160 PELLETS

*CLAIMS BASED ON TRADITIONAL HOMEOPATHIC PRACTICE, NOT ACCEPTED MEDICAL EVIDENCE. NOT FDA EVALUATED.
*C,K,CK, and X are homeopathic dilutions: see BoironUSA.com/info for details.